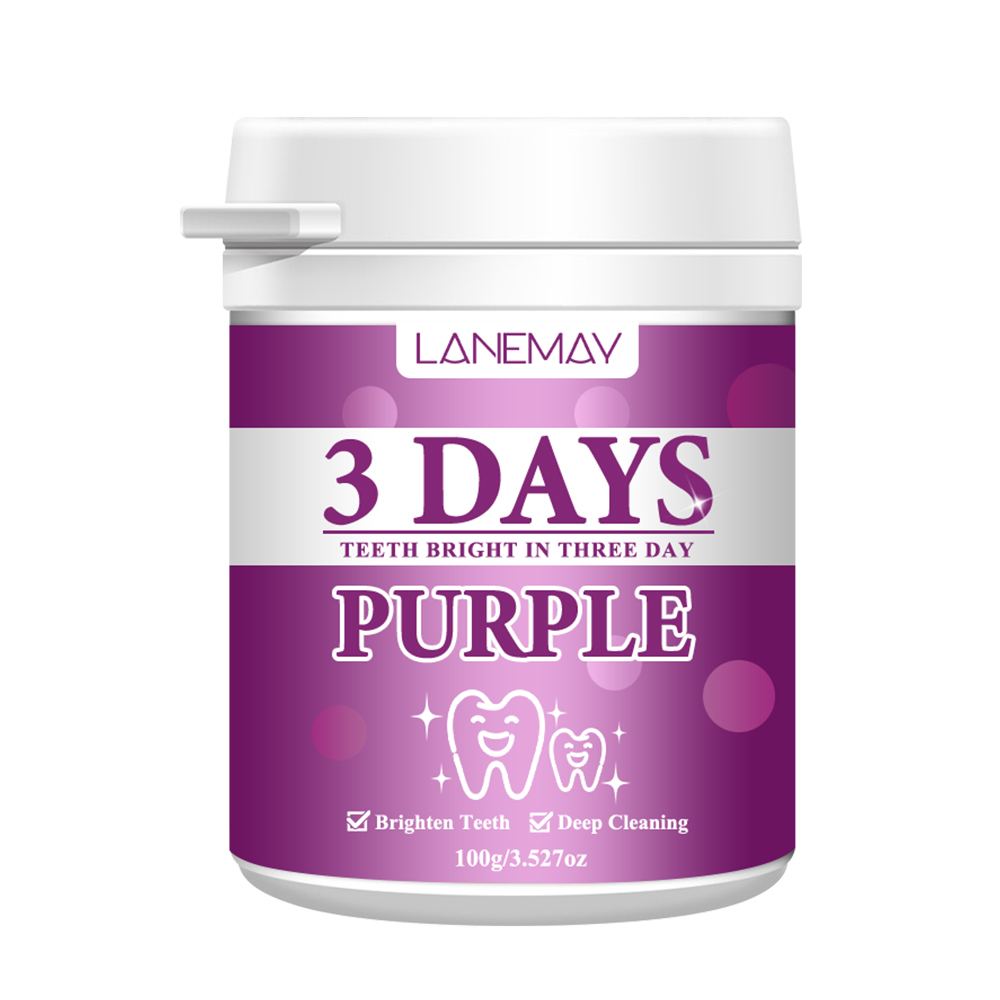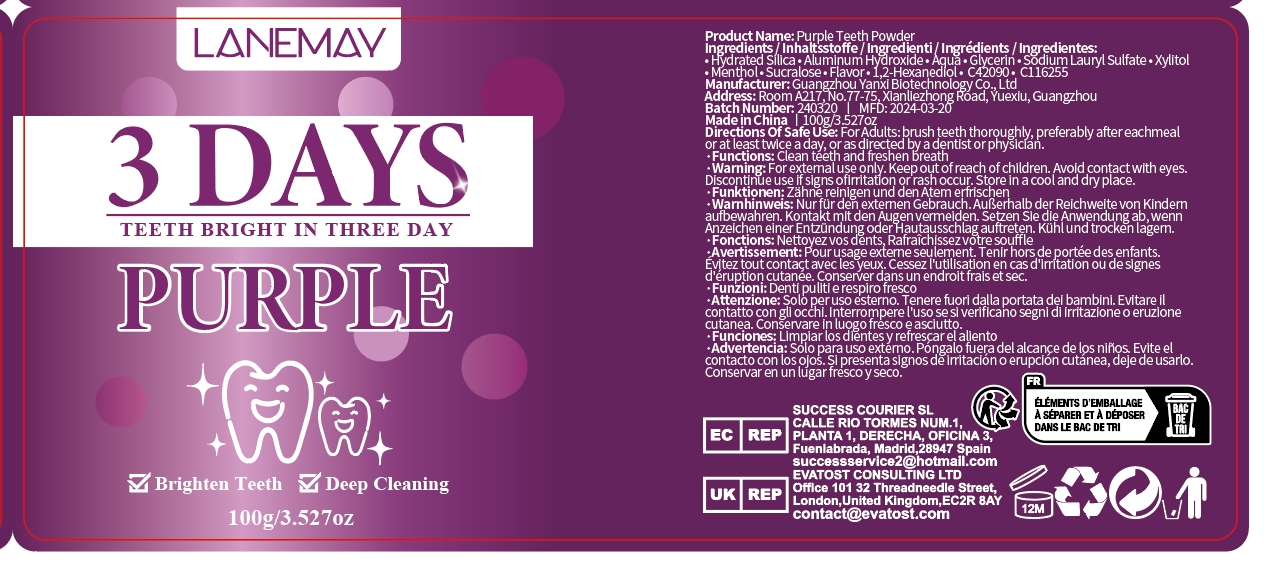 DRUG LABEL: Purple Teeth Powder
NDC: 84025-039 | Form: POWDER
Manufacturer: Guangzhou Yanxi Biotechnology Co., Ltd
Category: otc | Type: HUMAN OTC DRUG LABEL
Date: 20240603

ACTIVE INGREDIENTS: HYDRATED SILICA 5 mg/100 g; ALUMINUM HYDROXIDE 3 mg/100 g
INACTIVE INGREDIENTS: WATER

DOSAGE AND ADMINISTRATION

For Adults: brush teeth thoroughly, preferably after each meal or at least twice a day, or as directed by a dentist or physician.

WARNINGS

For external use only.

INDICATIONS AND USAGE

For Adults: brush teeth thoroughly, preferably after each meal or at least twice a day, or as directed by a dentist or physician.

Keep out of reach of children.

PURPOSE

Clean teeth and freshen breath

INACTIVE INGREDIENT

aqua